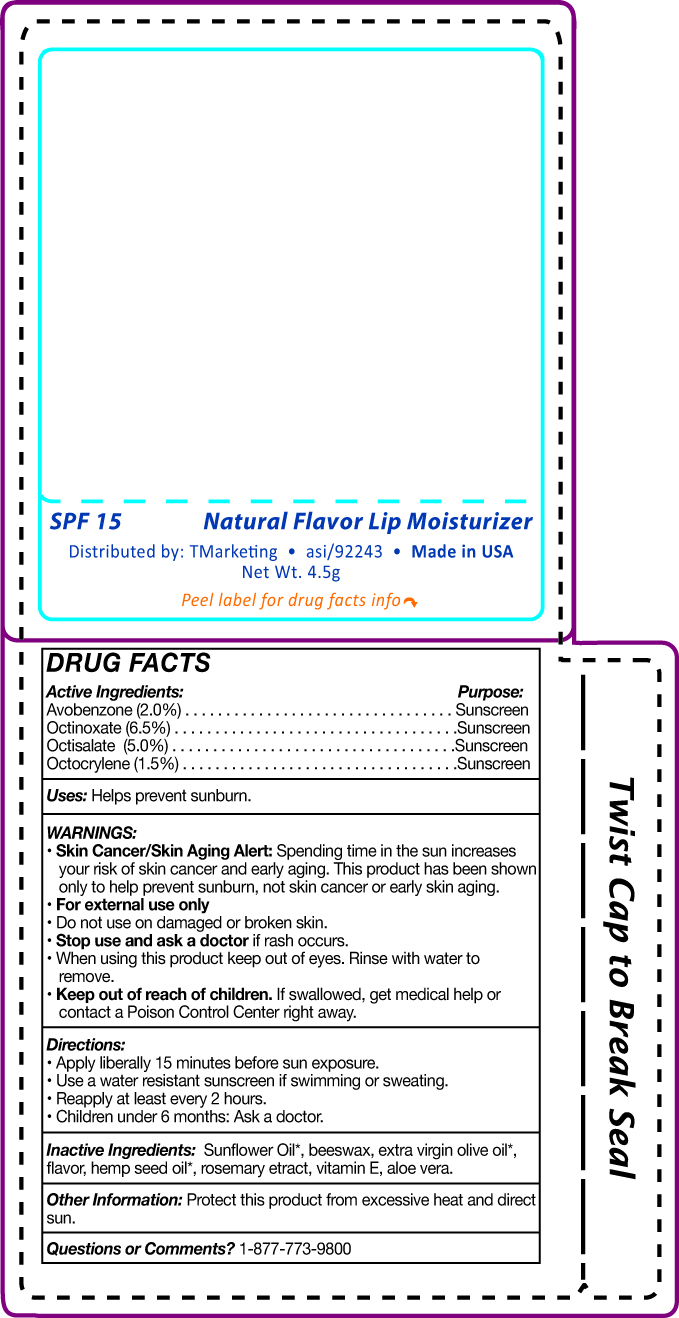 DRUG LABEL: Skin Crave spf15 lip balm
NDC: 58418-295 | Form: LIPSTICK
Manufacturer: Tropical Enterprises International, Inc.
Category: otc | Type: HUMAN OTC DRUG LABEL
Date: 20180711

ACTIVE INGREDIENTS: OCTOCRYLENE 1.5 mg/15 mL; OCTISALATE 5 mg/15 mL; AVOBENZONE 2 g/15 mL; OCTINOXATE 6.5 mg/15 mL
INACTIVE INGREDIENTS: SUNFLOWER OIL

spf15 lip balm

Active Ingredients: Purpose: Sunscreen

Avobenzone (2.0%)

Octinoxate (6.5%)

Octisalate (5.0%)

Octocrylene (1.5%)

Purpose: Sunscreen

INDICATIONS AND USAGE

Uses: Helps prevent sunburn

Warnings:

- Skin Cancer/Skin Aging Alert: Spending time in the sun increases your risk of skin cancer and early aging. Thois product has been shown only to help prevent sunburn, not skin cancer or early skin aging.
- For external use only
- Do not use on damaged or broken skin.

Stop use and ask a doctor if rash occurs.

- When using this product keep out of eyes. Rinse with water to remove.

- Keep out of reach of children. If swallowed, get medical help or contact a Poison Control Center right away.

Directions:

- Apply liberally 15 minutes before sun exposure.
- Use a water resistant sunscreen if swimming or sweating.
- Reapply at least every 2 hours.

INACTIVE INGREDIENT

Inactive Ingredients: Sunflower oil, beeswax, extra virgin olive oil, flavor, hemp seed oil, rosemaruy extract, vitamin E, aloe vera

Other Information: Protect this product from excessive heat and direct sun.

Questions or Comments? 1-877-773-9800